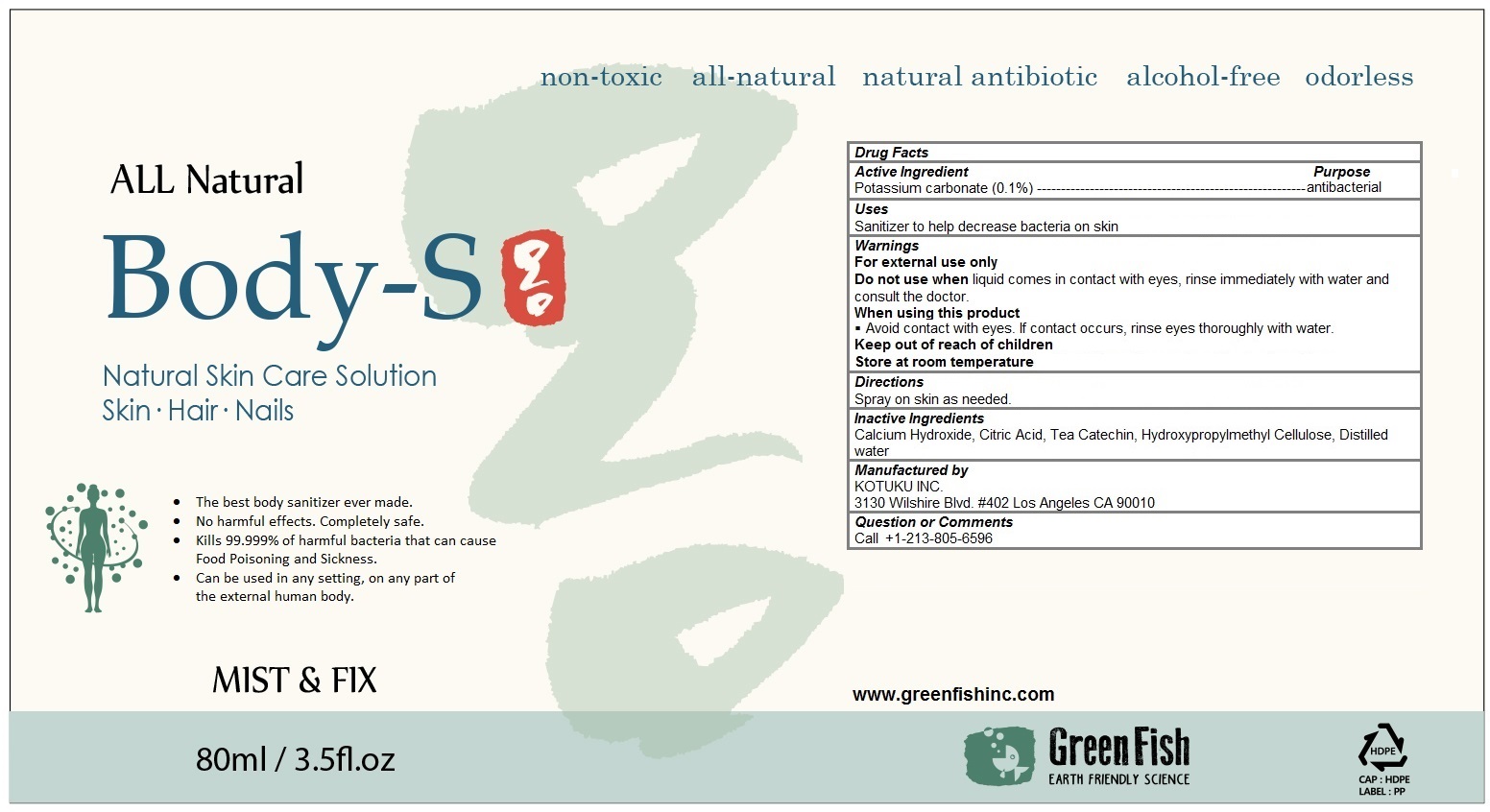 DRUG LABEL: Greenfish, Body-S
NDC: 70610-102 | Form: LIQUID
Manufacturer: KOTUKU INC.
Category: otc | Type: HUMAN OTC DRUG LABEL
Date: 20160418

ACTIVE INGREDIENTS: POTASSIUM CARBONATE 0.001 1/80 mL
INACTIVE INGREDIENTS: CITRIC ACID MONOHYDRATE; CALCIUM HYDROXIDE; HYPROMELLOSES; water

Greenfish, Body-S